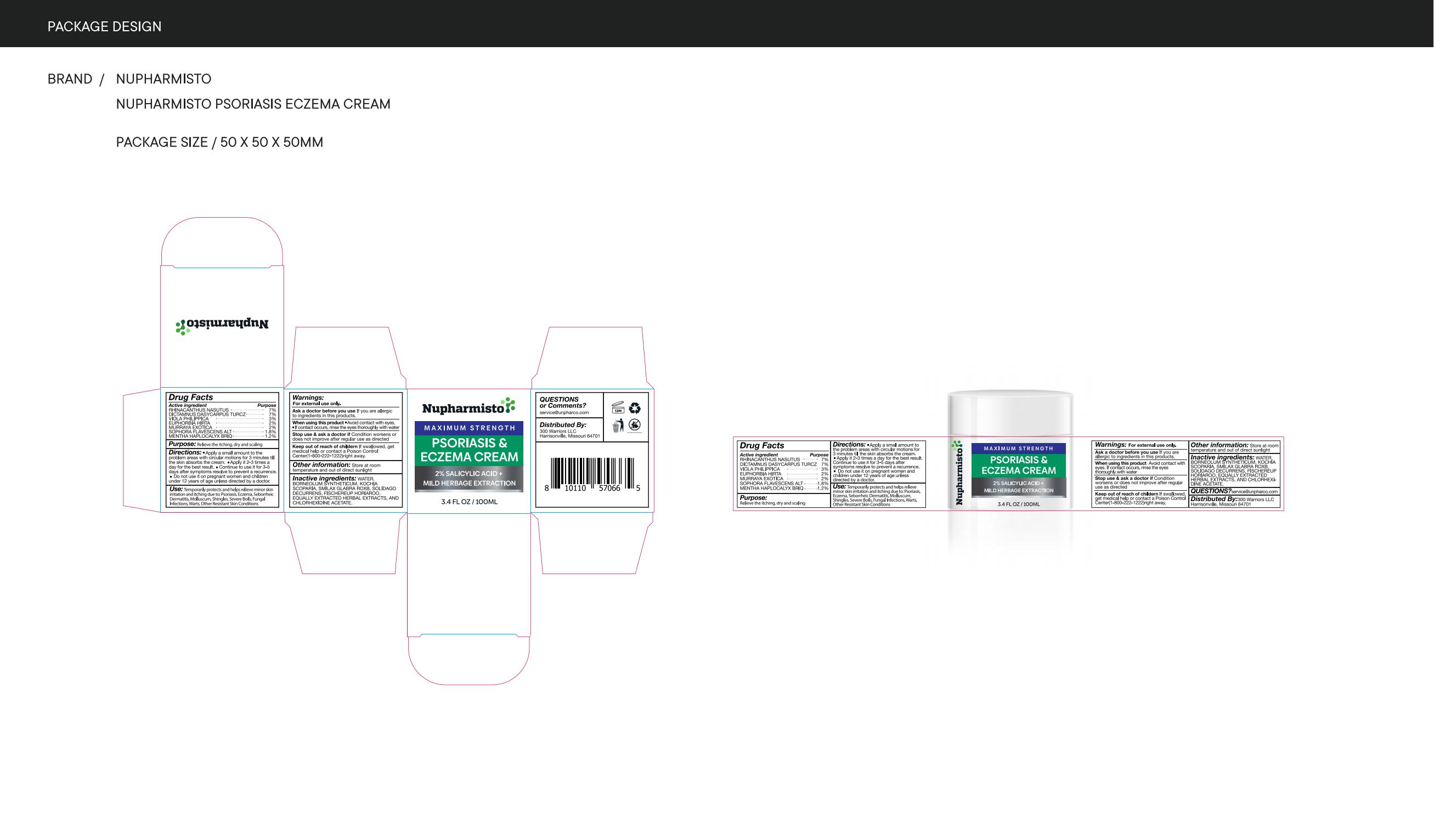 DRUG LABEL: Nupharmisto Psoriasis Eczema Cream
NDC: 81799-010 | Form: CREAM
Manufacturer: Ehy Holdings LLC
Category: otc | Type: HUMAN OTC DRUG LABEL
Date: 20230423

ACTIVE INGREDIENTS: MENTHA CANADENSIS TOP 1.2 mg/100 mL; VIOLA PHILIPPICA WHOLE 3 mg/100 mL; SOPHORA FLAVESCENS WHOLE 1.8 mg/100 mL; RHINACANTHUS NASUTUS LEAF 7 mg/100 mL; DICTAMNUS DASYCARPUS WHOLE 7 mg/100 mL; EUPHORBIA HIRTA 2 mg/100 mL; MURRAYA PANICULATA FRUIT 2 mg/100 mL
INACTIVE INGREDIENTS: BORNEOL; SMILAX GLABRA WHOLE; CHLORHEXIDINE ACETATE; SCOPARIA DULCIS LEAF; SOLIDAGO DECURRENS WHOLE; WATER

81799-010

Active Ingredient

RHINACANTHUS NASUTUS 7%
DICTAMNUS DASYCARPUS TURCZ 7%
VIOLA PHILIPPICA 3%
EUPHORBIA HIRTA 2%
MURRAYA EXOTICA 2%
SOPHORA FLAVESCENS ALT 1.8%
MENTHA HAPLOCALYX BRIQ 1.2%

Purpose

Relieve the itching, dry and scaling

Use

Temporarily protects and helps relieveminor skin irritation and itching due to: PsoriasisEczema, Seborrheic Dermatitis, Molluscum,Shingles, Severe Boils, Fungal lnfections, Warts.Other Resistant Skin Conditions

Warnings

For external use only.

WHEN USING SECTION

Avoid contact with eyeslf contact occurs, rinse the eyes thoroughly with water

STOP USE section

Condition worsens ordoes not improve after regular use as directed

KEEP OUT OF REACH OF CHILDREN

If swallowed, getmedical help or contact aPoison Control Center(1-800-222-1222) right away.

ASK DOCTOR

Apply a thin layer over the affected areatwice daily(morning and night), or asdirected by a doctor.
If the condition persists longer, consult a doctor.

Directions

Apply a small amount to theproblem areas with circularmotions for 3 minutes till theskin absorbs the cream.

Other information

Store at 59-86ff(15-30°CClose the cap tightly after use.

Inactive ingredients

Smilax Glabra, Sophora Flavescens, CnidiumMonnier(L) Cuss, Fructus Kochiae, Pseudolarixamabillis, Cortex Dictamni, Stemonatuberosalour, Mentha, Glycyrrhetinic Acid

PACKAGE LABEL - PRINCIPAL DISPLAY PANEL

81799-010-01